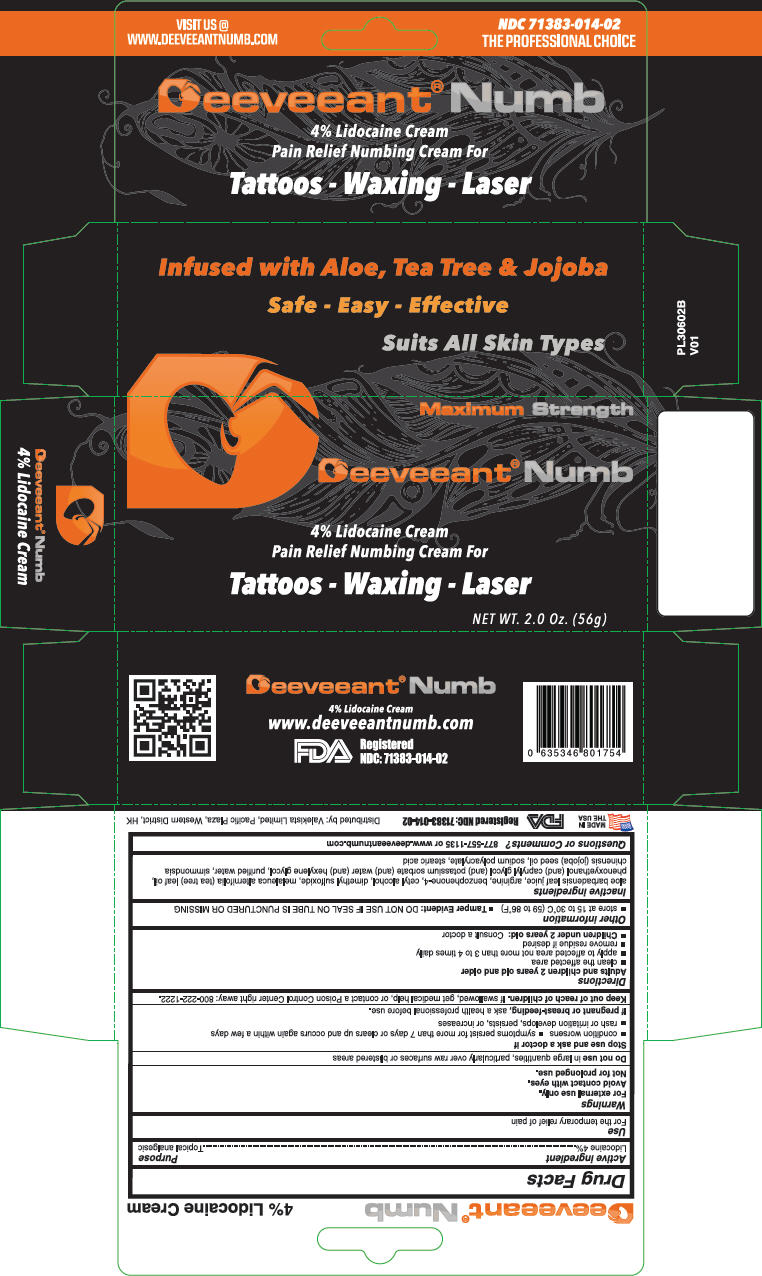 DRUG LABEL: Deeveeant Numb
NDC: 71383-014 | Form: CREAM
Manufacturer: Valekista Limited
Category: otc | Type: HUMAN OTC DRUG LABEL
Date: 20170706

ACTIVE INGREDIENTS: Lidocaine 40 mg/1 g
INACTIVE INGREDIENTS: Aloe Vera Leaf; Arginine; Sulisobenzone; Cetyl Alcohol; Dimethyl Sulfoxide; Tea Tree Oil; Phenoxyethanol; Caprylyl Glycol; Potassium Sorbate; Hexylene Glycol; Water; Jojoba Oil; Sodium Polyacrylate (2500000 MW); Stearic Acid

Deeveeant® Numb

Active Ingredient

Lidocaine 4%

Purpose

Topical Analgesic

Use

For the temporary relief of pain

Warnings

For external use only

WHEN USING

Avoid contact with eyes

Not for prolonged use

Do not use in large quantities, particularly over raw surfaces or blistered areas

Stop use and ask a doctor if

- condition worsens
- symptoms persist for more than 7 days or clears up and occurs again within a few days
- rash or irritation develops, persists or increases

PREGNANCY OR BREAST FEEDING

If pregnant or breast-feeding, ask a health professional before use.

Keep out of reach of children. If swallowed, get medical help, or contact a Poison Control Center right away: 800-222-1222

Directions

Adults and children 2 years and older

- clean the affected area
- apply to affected area not more than 3 to 4 times daily
- remove residue if desired
- Children under 2 years old: Consult a doctor

Other information

- Store at 15 to 30°C (59 to 86°F)
- Tamper Evident: DO NOT USE IF SEAL ON TUBE IS PUNCTURED OR MISSING

Inactive ingredients

Aloe barbadensis leaf juice, arginine, benzophenone-4, cetyl alcohol, dimethyl sulfoxide, melaleuca alternifolia (tea tree) leaf oil, phenoxyethanol; (and) caprylyl glycol (and) potassium sorbate (and) water (and) hexylene glycol, purified water, simmondsia chinensis (jojoba) seed oil, sodium polyacrylate, stearic acid

Questions or Comments?

877-557-1135 or www.deeveeantnumb.com

Distributed by: Valekista Limited, Pacific Plaza, Western District, HK

PRINCIPAL DISPLAY PANEL - 56 g Tube Box

Maximum Strength

Deeveeant® Numb

4% Lidocaine Cream
Pain Relief Numbing Cream For

Tattoos - Waxing - Laser

NET WT. 2.0 Oz. (56g)